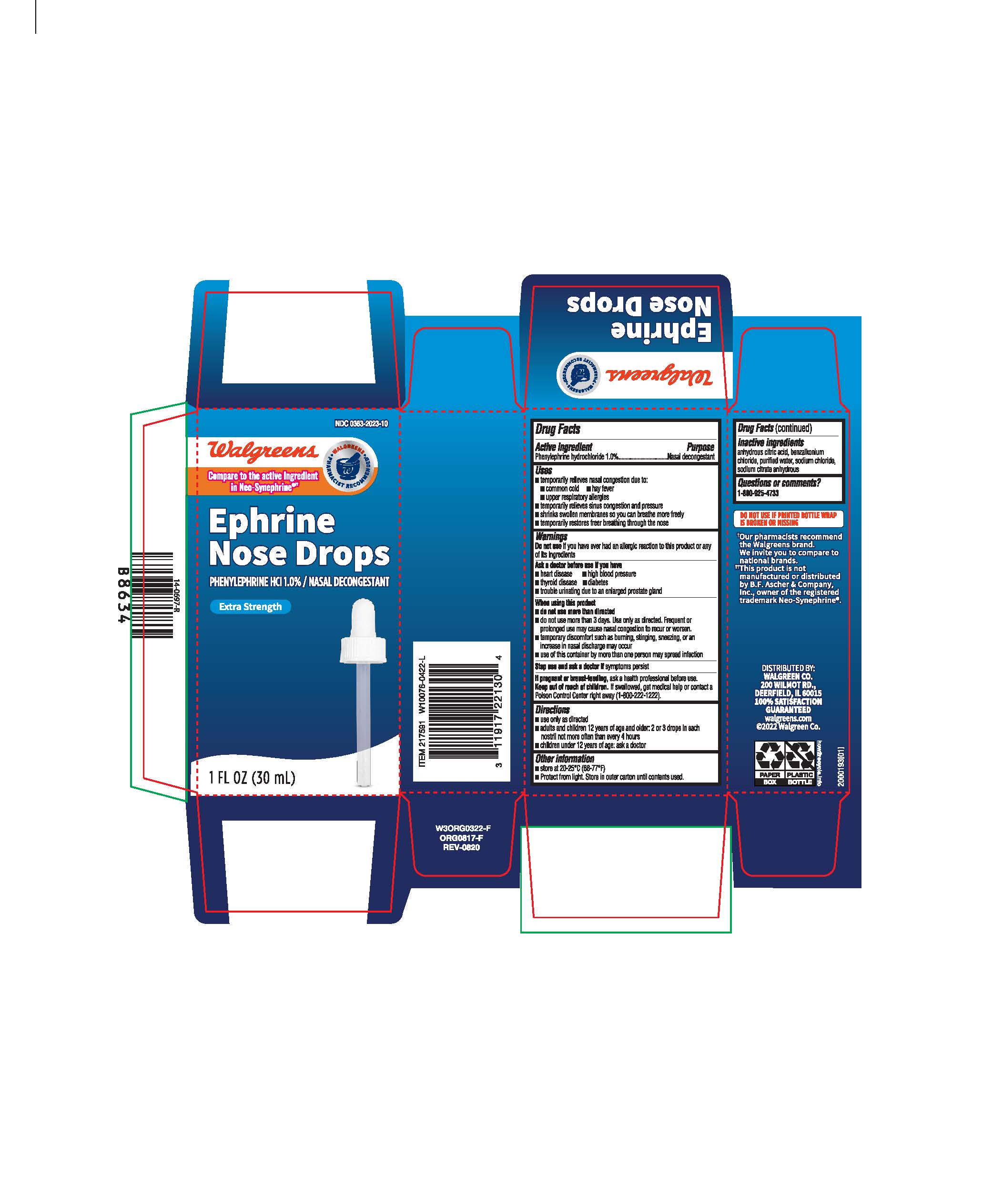 DRUG LABEL: Ephrine Nose Drops
NDC: 0363-2023 | Form: SOLUTION/ DROPS
Manufacturer: Walgreens
Category: otc | Type: HUMAN OTC DRUG LABEL
Date: 20231031

ACTIVE INGREDIENTS: PHENYLEPHRINE HYDROCHLORIDE 1 g/100 mL
INACTIVE INGREDIENTS: SODIUM CITRATE; WATER; SODIUM CHLORIDE; BENZALKONIUM CHLORIDE; ANHYDROUS CITRIC ACID

Walgreens ephrine nose drops

Active Ingredient

Phenylephrine hydrochloride 1.0%

Purpose

Nasal decongestant

Uses

temporarily relieves nasal congestion due to:
•common cold
•hay fever
•upper respiratory allergies
•temporarily relieves sinus congestion and pressure
•shrinks swollen membranes so you can breathe more freely
•temporarily restores freer breathing through the nose

Warnings

Do not use

if you have ever had an allergic reaction to this product or any of its ingredients

Ask a doctor before use if you have

•heart disease
•high blood pressure
•thyroid disease
•diabetes
•trouble urinating due to an enlarged prostate gland

When using this product

•do not use more than directed
•do not use for more than 3 days. Use only as directed. Frequent or prolonged use may cause nasal congestion to recur or worsen.
•temporary discomfort such as burning, stinging, sneezing, or an increase in nasal discharge may occur
•use of this container by more than one person may spread infection

Stop use and ask a doctor if

symptoms persist

If pregnant or breast-feeding,

ask a health professional before use.

Keep out of reach of children

If swallowed, get medical help or contact a Poison Control Center right away (1-800-222-1222).

Directions

•use only as directed
•adults and children 12 years of age and older: 2 or 3 drops in each nostril not more often than every 4 hours
•children under 12 years of age: ask a doctor

Other information

•store at 20-25°C (68-77°F)
•Protect from light. Store in outer carton until contents used.

Inactive Ingredients

anhydrous citric acid, benzalkonium chloride solution, purified water, sodium chloride, sodium citrate

Questions or comments ?

1-800-925-4733

Principal Display Panel (carton)

Compare to Neo-Synephrine® active ingredient

Ephrine Nose Drops

PHENYLEPHRINE HCl 1.0% / NASAL DECONGESTANT

EXTRA STRENGTH

Fast relief

1 FL OZ (30 mL)